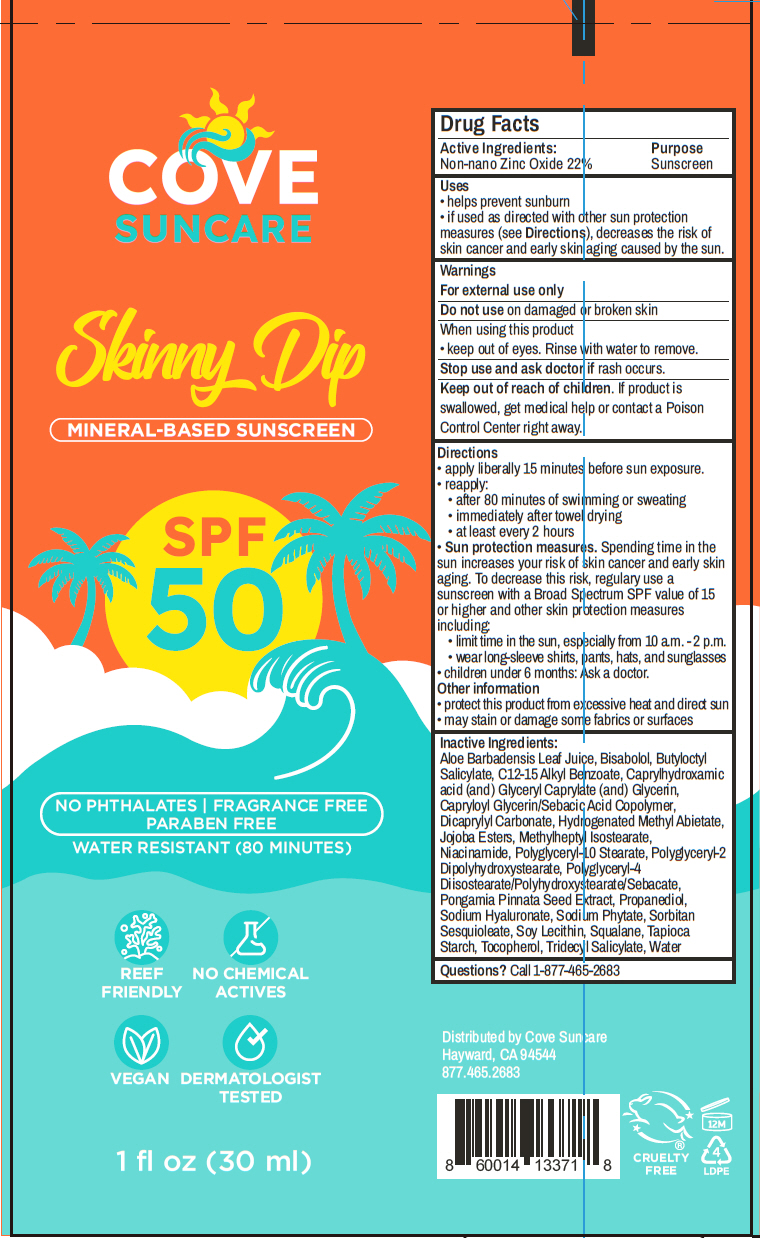 DRUG LABEL: Skinny Dip SPF-50
NDC: 85753-103 | Form: LOTION
Manufacturer: Cove Suncare LLC
Category: otc | Type: HUMAN OTC DRUG LABEL
Date: 20251008

ACTIVE INGREDIENTS: Zinc Oxide 22 g/100 mL
INACTIVE INGREDIENTS: WATER; Butyloctyl Salicylate; Tridecyl Salicylate; ALKYL (C12-15) BENZOATE; Dicaprylyl Carbonate; Propanediol; Methylheptyl Isostearate; Polyglyceryl-10 Stearate; Hydrogenated Methyl Abietate; CAPRYLOYL GLYCERIN/SEBACIC ACID COPOLYMER (2000 MPA.S); Polyglyceryl-4 Diisostearate/Polyhydroxystearate/Sebacate; ALOE VERA LEAF JUICE; Polyglyceryl-2 Dipolyhydroxystearate; Caprylhydroxamic acid; GLYCERYL MONOCAPRYLATE; Glycerin; SOYBEAN LECITHIN; Sorbitan Sesquioleate; STARCH, TAPIOCA; PONGAMIA PINNATA SEED; Tocopherol; LEVOMENOL; PHYTATE SODIUM; Squalane; Niacinamide; HYALURONATE SODIUM

Skinny Dip SPF-50

Drug Facts

Active Ingredients

Non-nano Zinc Oxide 22%

Purpose

Sunscreen

Uses

- helps prevent sunburn
- if used as directed with other sun protection measures (see Directions), decreases the risk of skin cancer and early skin aging caused by the sun.

Warnings

For external use only

Do not use on damaged or broken skin

When using this product

- keep out of eyes. Rinse with water to remove.

Stop use and ask doctor if rash occurs.

Keep out of reach of children. If product is swallowed, get medical help or contact a Poison Control Center right away.

Directions

- apply liberally 15 minutes before sun exposure.
- reapply:
  - after 80 minutes of swimming or sweating
  - immediately after towel drying
  - at least every 2 hours
- Sun protection measures. Spending time in the sun increases your risk of skin cancer and early skin aging. To decrease this risk, regulary use a sunscreen with a Broad Spectrum SPF value of 15 or higher and other skin protection measures including:
  - limit time in the sun, especially from 10 a.m. - 2 p.m.
  - wear long-sleeve shirts, pants, hats, and sunglasses
- children under 6 months: Ask a doctor.

Other information

- protect this product from excessive heat and direct sun
- may stain or damage some fabrics or surfaces

Inactive Ingredients

Aloe Barbadensis Leaf Juice, Bisabolol, Butyloctyl Salicylate, C12-15 Alkyl Benzoate, Caprylhydroxamic acid (and) Glyceryl Caprylate (and) Glycerin, Capryloyl Glycerin/Sebacic Acid Copolymer, Dicaprylyl Carbonate, Hydrogenated Methyl Abietate, Jojoba Esters, Methylheptyl Isostearate, Niacinamide, Polyglyceryl-10 Stearate, Polyglyceryl-2 Dipolyhydroxystearate, Polyglyceryl-4 Diisostearate/Polyhydroxystearate/Sebacate, Pongamia Pinnata Seed Extract, Propanediol, Sodium Hyaluronate, Sodium Phytate, Sorbitan Sesquioleate, Soy Lecithin, Squalane, Tapioca Starch, Tocopherol, Tridecyl Salicylate, Water

Questions?

Call 1-877-465-2683

Distributed by Cove Suncare
Hayward, CA 94544

PRINCIPAL DISPLAY PANEL - 30 ml Tube Label

COVE
SUNCARE

Skinny Dip

MINERAL-BASED SUNSCREEN

SPF
50

NO PHTHALATES | FRAGRANCE FREE
PARABEN FREE

WATER RESISTANT (80 MINUTES)

REEF
FRIENDLY

NO CHEMICAL
ACTIVES

VEGAN

DERMATOLOGIST
TESTED

1 fl oz (30 ml)